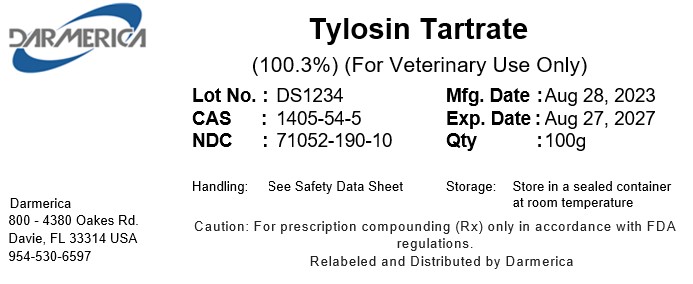 DRUG LABEL: Tylosin Tartrate
NDC: 71052-190 | Form: POWDER
Manufacturer: DARMERICA, LLC
Category: other | Type: BULK INGREDIENT - ANIMAL DRUG
Date: 20241226

ACTIVE INGREDIENTS: Tylosin Tartrate 1 kg/1 kg

Tylosin Tartrate